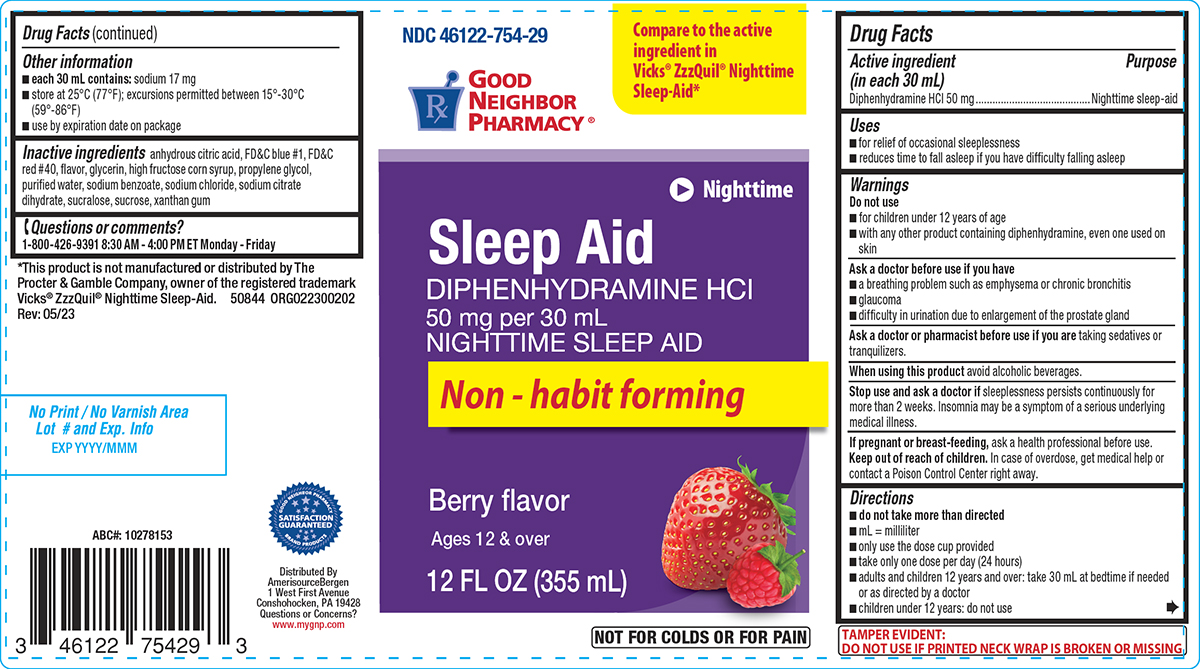 DRUG LABEL: Sleep Aid
NDC: 46122-754 | Form: SOLUTION
Manufacturer: Amerisource Bergen
Category: otc | Type: HUMAN OTC DRUG LABEL
Date: 20251021

ACTIVE INGREDIENTS: DIPHENHYDRAMINE HYDROCHLORIDE 50 mg/30 mL
INACTIVE INGREDIENTS: ANHYDROUS CITRIC ACID; FD&C BLUE NO. 1; FD&C RED NO. 40; GLYCERIN; HIGH FRUCTOSE CORN SYRUP; PROPYLENE GLYCOL; WATER; SODIUM BENZOATE; SODIUM CHLORIDE; TRISODIUM CITRATE DIHYDRATE; SUCRALOSE; SUCROSE; XANTHAN GUM

Good Neighbor Pharmacy 44-002A

Active ingredient (in each 30 mL)

Diphenhydramine HCl 50 mg

Purpose

Nighttime sleep-aid

Uses

- for relief of occasional sleeplessness
- reduces time to fall asleep if you have difficulty falling asleep

Warnings

Do not use

- for children under 12 years of age
- with any other product containing diphenhydramine, even one used on skin

Ask a doctor before use if you have

- a breathing problem such as emphysema or chronic bronchitis
- glaucoma
- difficulty in urination due to enlargement of the prostate gland

Ask a doctor or pharmacist before use if you are

taking sedatives or tranquilizers.

When using this product

avoid alcoholic beverages.

Stop use and ask a doctor if

sleeplessness persists continuously for more than 2 weeks. Insomnia may be a symptom of a serious underlying medical illness.

If pregnant or breast-feeding,

ask a health professional before use.

Keep out of reach of children.

In case of overdose, get medical help or contact a Poison Control Center right away.

Directions

- do not take more than directed
- mL = milliliter
- only use the dose cup provided
- take only one dose per day (24 hours)
- adults and children 12 years and over: take 30 mL at bedtime if needed or as directed by a doctor
- children under 12 years: do not use

Other information

- each 30 mL contains: sodium 17 mg
- store at 25°C (77°F); excursions permitted between 15°-30°C (59°-86°F)
- use by expiration date on package

Inactive ingredients

anhydrous citric acid, FD&C blue #1, FD&C red #40, flavor, glycerin, high fructose corn syrup, propylene glycol, purified water, sodium benzoate, sodium chloride, sodium citrate dihydrate, sucralose, sucrose, xanthan gum

Questions or comments?

1-800-426-9391 8:30 AM - 4:00 PM ET Monday - Friday

Principal display panel

NDC 46122-754-29

GOOD
NEIGHBOR
PHARMACY®

Compare to the active
ingredient in
Vicks® ZzzQuil® Nighttime
Sleep-Aid*

Nighttime

Sleep Aid
DIPHENHYDRAMINE HCl
50 mg per 30 mL
NIGHTTIME SLEEP AID

Non - habit forming

Berry flavor

Ages 12 & over

12 FL OZ (355 mL)

NOT FOR COLDS OR FOR PAIN

TAMPER EVIDENT:
DO NOT USE IF PRINTED NECK WRAP IS BROKEN OR MISSING

*This product is not manufactured or distributed by The
Procter & Gamble Company, owner of the registered trademark
Vicks® ZzzQuil® Nighttime Sleep-Aid. 50844 ORG022300202
Rev: 05/23

Distributed By
AmerisourceBergen
1 West First Avenue
Conshohocken, PA 19428
Questions or Concerns?
www.mygnp.com

Good Neighbor Pharmacy 44-002A